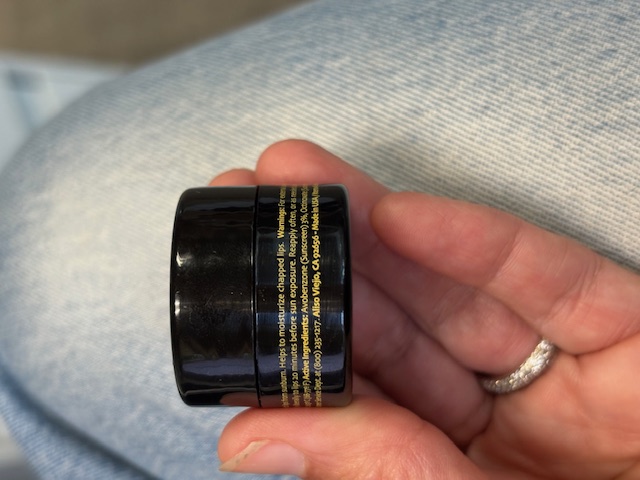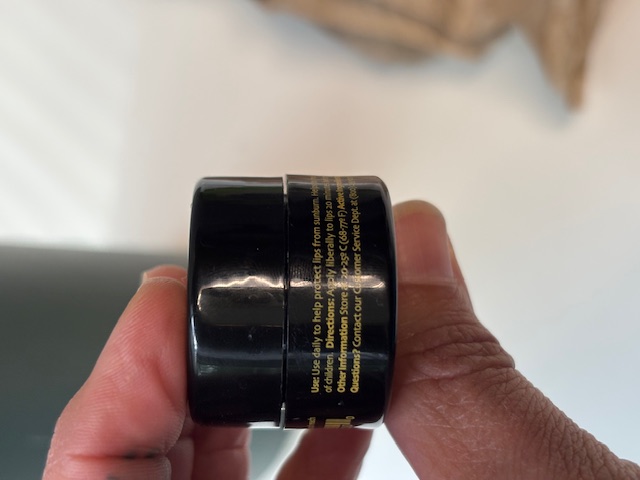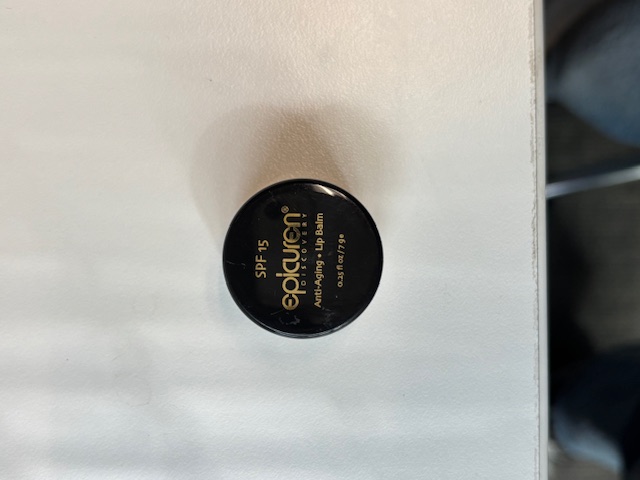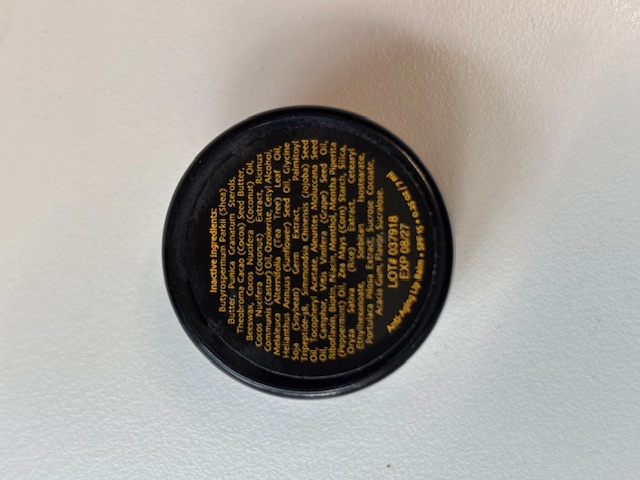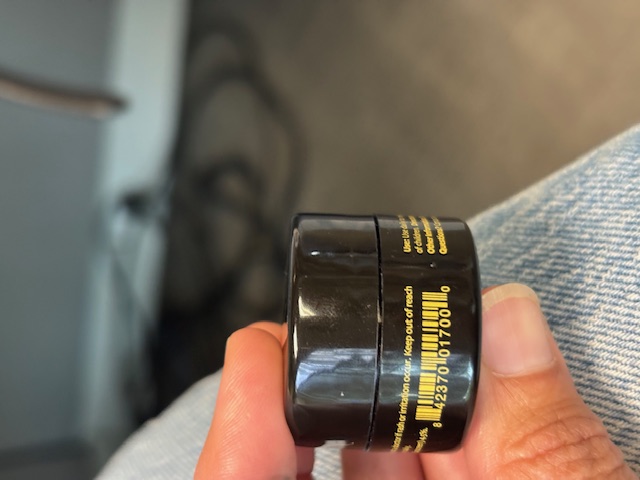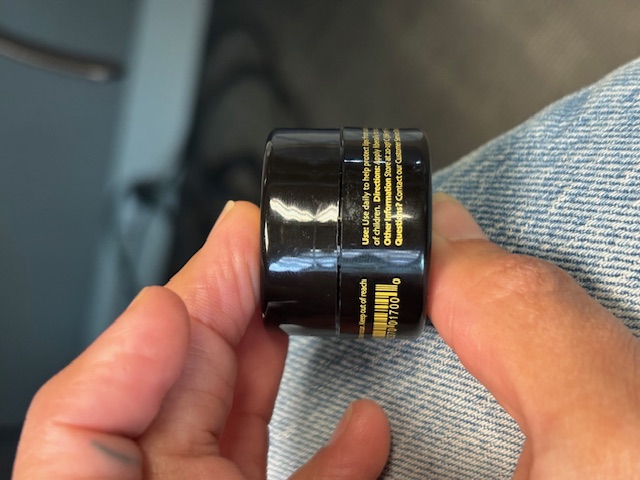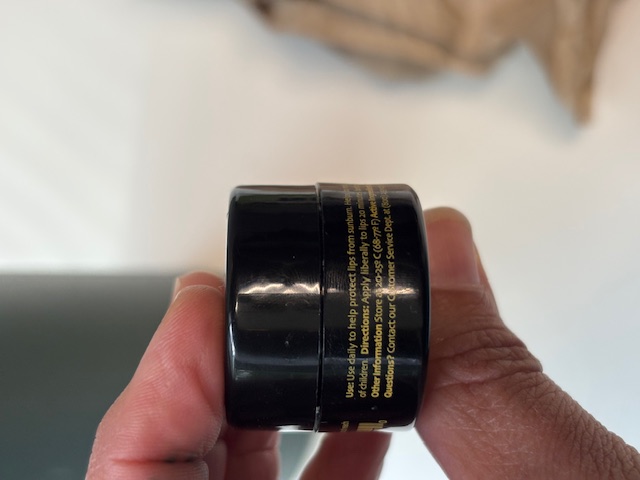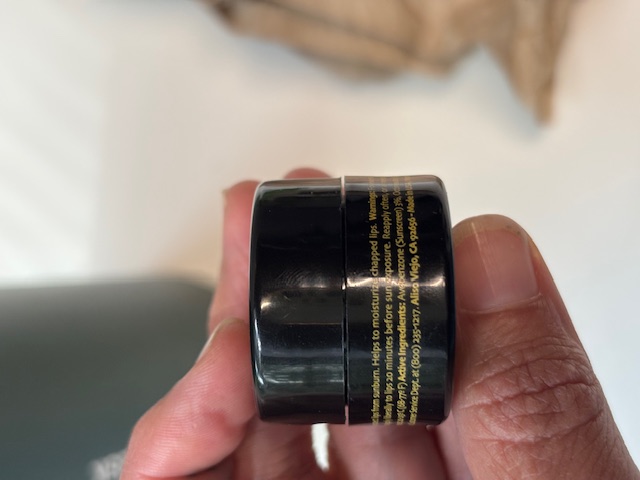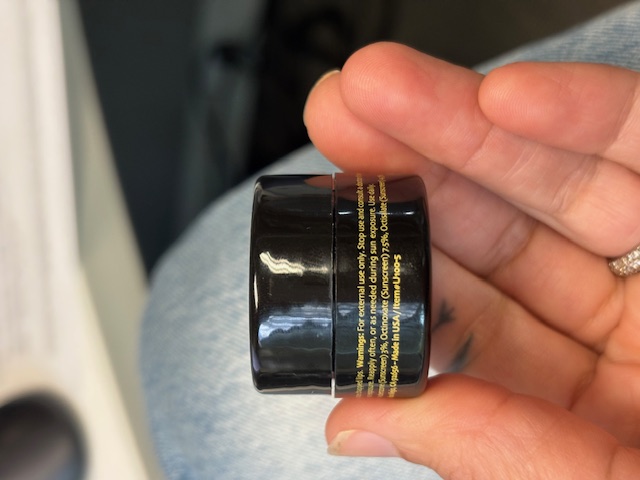 DRUG LABEL: Anti Aging Lip Balm Pot SPF 15
NDC: 84378-103 | Form: OINTMENT
Manufacturer: Epicuren Disocovery
Category: otc | Type: HUMAN OTC DRUG LABEL
Date: 20251007

ACTIVE INGREDIENTS: AVOBENZONE 3 g/100 g; OCTISALATE 4.5 g/100 g; OCTINOXATE 7.5 g/100 g
INACTIVE INGREDIENTS: MELALEUCA ALTERNIFOLIA (TEA TREE) LEAF OIL; PALMITOYL TRIPEPTIDE-38; ALEURITES MOLUCCANUS SEED OIL; RIBOFLAVIN; BIOTIN; SILICA; ORYZA SATIVA (RICE) STARCH; CETEARYL ETHYLHEXANOATE; .ALPHA.-TOCOPHEROL ACETATE; CAMPHOR (NATURAL); CETYL ALCOHOL; ACACIA; GLYCINE SOJA (SOYBEAN) SEED; MENTHA PIPERITA (PEPPERMINT) OIL; HELIANTHUS ANNUUS (SUNFLOWER) SEED OIL; RICINUS COMMUNIS (CASTOR) SEED OIL; VITIS VINIFERA (GRAPE) SEED OIL; FLAVOR SPICE MINT N&A110589; SUCRALOSE; COCOS NUCIFERA (COCONUT) FRUIT; SIMMONDSIA CHINENSIS (JOJOBA) SEED OIL; NIACIN; ZEA MAYS (CORN) STARCH; MENTHOL; SORBITAN ISOSTEARATE; SUCROSE COCOATE; PORTULACA PILOSA WHOLE; BUTYROSPERMUM PARKII (SHEA) BUTTER UNSAPONIFIABLES; PUNICA GRANATUM STEROLS; COCOS NUCIFERA (COCONUT) OIL; THEOBROMA CACAO (COCOA) SEED BUTTER; CERESIN

Anti-Aging Lip Balm Pot SPF 15